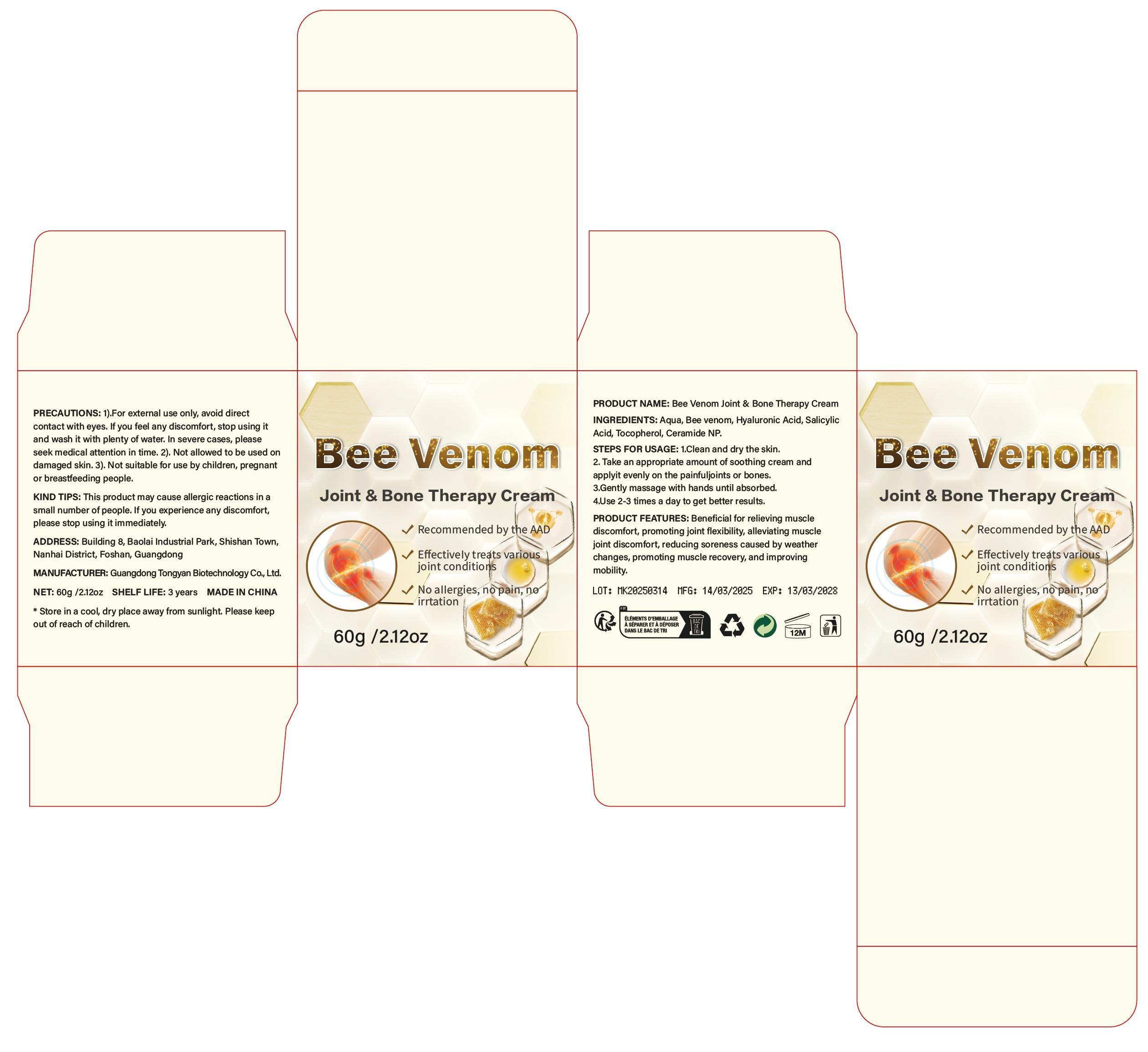 DRUG LABEL: Bee Venom Joint Bone Therapy Cream
NDC: 85594-007 | Form: CREAM
Manufacturer: Dongguan Haiyi Cosmetics Co., Ltd.
Category: otc | Type: HUMAN OTC DRUG LABEL
Date: 20250722

ACTIVE INGREDIENTS: APIS MELLIFERA VENOM 6 mg/100 g
INACTIVE INGREDIENTS: CERAMIDE NP; HYALURONIC ACID; SALICYLIC ACID; TOCOPHEROL; AQUA

85594-007-60 Bee Venom Joint & Bone Therapy Cream

ACTIVE INGREDIENT

Bee venom

INACTIVE INGREDIENT

Aqua,Hyaluronic Acid, SalicylicAcid, Tocopherol, Ceramide NP.

PURPOSE

Recommended by the AAD
Effectively treats variousjoint conditions
No allergies, nopain, neirrtation

WARNINGS

This product may cause allergic reactions in asmall number of people. lf you experience any discomfort,please stop using it immediately.

STOP USE

This product may cause allergic reactions in asmall number of people.
lf youexperience any discomfort,please stop using it immediately.

DO NOT USE

Not suitable for use by children, pregnantor breast feeding people.

KEEP OUT OF REACH OF CHILDREN

KEEP THE PRODUCT OUT OF REACH OF CHILDREN to

INDICATIONS AND USAGE

1.Clean and dry the skin.

2.Take an appropriate amount of soothing cream andapplyit evenly on the painfuljoints or bones.

3.Gently massage with hands until absorbed.

4.Use 2-3 times a day to get better results.

DOSAGE AND ADMINISTRATION

Use 2-3 times a day to get better results.